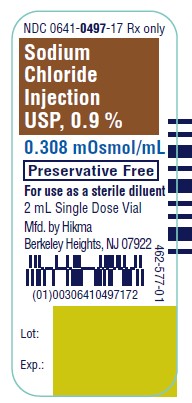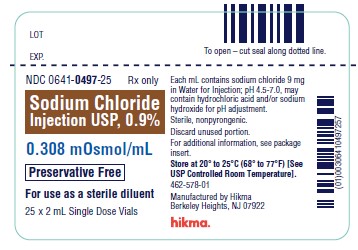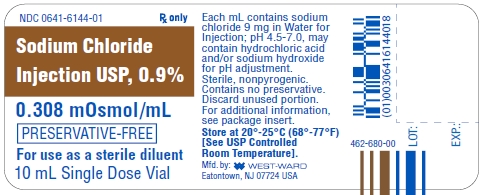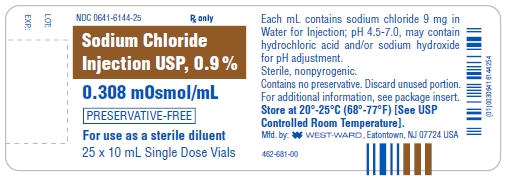 DRUG LABEL: Sodium Chloride
NDC: 0641-0497 | Form: INJECTION
Manufacturer: Hikma Pharmaceuticals USA Inc.
Category: prescription | Type: HUMAN PRESCRIPTION DRUG LABEL
Date: 20240410

ACTIVE INGREDIENTS: SODIUM CHLORIDE 9 mg/1 mL
INACTIVE INGREDIENTS: SODIUM HYDROXIDE; HYDROCHLORIC ACID; WATER

Sodium Chloride Injection USP, 0.9%

Rx only

DESCRIPTION

This preparation is designed solely for parenteral use only after addition of drugs that require dilution or must be dissolved in an aqueous vehicle prior to injection.

Sodium Chloride Injection USP, 0.9% is a sterile, nonpyrogenic, isotonic solution of sodium chloride and water for injection. Each mL contains sodium chloride 9 mg. It contains no bacteriostat, antimicrobial agent or added buffer and is supplied only in single-dose containers to dilute or dissolve drugs for injection. Its chloride and sodium ion concentrations are approximately 0.154 mEq of each per milliliter and its calculated osmolality is 0.308 milliosmols per mL. The solution may contain hydrochloric acid and/or sodium hydroxide for pH adjustment, pH 5.3 (4.5 to 7.0).

Sodium chloride, USP occurs as colorless cubic crystals or white crystalline powder and has a saline taste. Sodium chloride is freely soluble in water. The empirical formula for sodium chloride is NaCl, and the molecular weight is 58.44.

CLINICAL PHARMACOLOGY

Sodium chloride in water dissociates to provide sodium (Na^+) and chloride (Cl^–) ions. These ions are normal constituents of the body fluids (principally extracellular) and are essential for maintaining electrolyte balance.

The distribution and excretion of sodium (Na^+) and chloride (Cl^–) are largely under the control of the kidney which maintains a balance between intake and output. The small volume of fluid and amount of sodium chloride provided by Sodium Chloride Injection USP, 0.9% when used only as an isotonic vehicle for parenteral injection of drugs, is unlikely to exert a significant effect on fluid and electrolyte balance except possibly in neonates and very small infants.

Water is an essential constituent of all body tissues and accounts for approximately 70% of total body weight. Average normal adult daily requirement ranges from two to three liters (1.0 to 1.5 liters each for insensible water loss by perspiration and urine production).

Water balance is maintained by various regulatory mechanisms. Water distribution depends primarily on the concentration of electrolytes in the body compartments and sodium (Na^+) plays a major role in maintaining physiologic equilibrium.

INDICATIONS AND USAGE

This parenteral preparation indicated only for diluting or dissolving drugs for intravenous, intramuscular or subcutaneous injection, according to instructions of the manufacturer of the drug to be administered.

PRECAUTIONS

General

Consult the manufacturer’s instructions for choice of vehicle, appropriate dilution or volume for dissolving the drugs to be injected, including the route and rate of injection.

Inspect reconstituted (diluted or dissolved) drugs for clarity (if soluble) and freedom from unexpected precipitation or discoloration prior to administration.

Pregnancy

Pregnancy Category C

Animal reproduction studies have not been conducted with Sodium Chloride Injection USP, 0.9%. It is also not known whether sodium chloride injection containing additives can cause fetal harm when administered to a pregnant woman or can affect reproduction capacity. Sodium chloride injection containing additives should be given to a pregnant woman only if clearly needed.

Pediatric Use

The safety and effectiveness in the pediatric population are based on the similarity of the clinical conditions of the pediatric and adult populations. In neonates or very small infants the volume of fluid may affect fluid and electrolyte balance.

Drug Interactions

Some drugs for injection may be incompatible in a given vehicle, or when combined in the same vehicle or in a vehicle containing benzyl alcohol.

Consult with pharmacist, if available. Use aseptic technique for entry and withdrawal from all containers.

When diluting or dissolving drugs, mix thoroughly and use promptly.

Do not store reconstituted solutions of drugs for injection unless otherwise directed by the manufacturer of the solute.

Do not use unless the solution is clear and seal intact. Do not reuse single dose containers, discard unused portion.

ADVERSE REACTIONS

Reactions which may occur because of this solution, added drugs or the technique of reconstitution or administration include febrile response, local tenderness, abscess, tissue necrosis or infection at the site of injection, venous thrombosis or phlebitis extending from the site of injection and extravasation.

If an adverse reaction does occur, discontinue the infusion, evaluate the patient, institute appropriate countermeasures, and if possible, retrieve and save the remainder of the unused vehicle for examination.

OVERDOSAGE

Use only as a diluent or solvent. This parenteral preparation is unlikely to pose a threat of carbohydrate, sodium chloride or fluid overload except possibly in neonates or very small infants. In the event these should occur, re-evaluate the patient and institute appropriate corrective measures. See PRECAUTIONS and ADVERSE REACTIONS.

DOSAGE AND ADMINISTRATION

The volume of the preparation to be used for diluting or dissolving any drug for injection, is dependent on the vehicle concentration, dose and route of administration as recommended by the manufacturer.

This parenteral should be inspected visually for particulate matter and discoloration prior to administration, whenever solution and container permit.

HOW SUPPLIED

Sodium Chloride Injection USP, 0.9% is supplied in the following:

2 mL vials packaged in carton of 25 vials (NDC 0641-0497-25)

10 mL vials packaged in carton of 25 vials (NDC 0641-6144-25)

Storage

Store at 20° - 25°C (68°-77°F), excursions permitted to 15° - 30°C (59° - 86°F) [See USP Controlled Room Temperature]. Avoid freezing.

To report SUSPECTED ADVERSE REACTIONS, contact Hikma Pharmaceuticals USA Inc. at 1-877-845-0689, or the FDA at 1-800-FDA-1088 or www.fda.gov/medwatch.

For Product Inquiry call 1-877-845-0689.

Manufactured by:

Hikma Pharmaceuticals USA Inc.

Berkeley Heights, NJ 07922

Revised August 2020

462-679-0

PRINCIPAL DISPLAY PANEL

NDC 0641-0497-17 Rx only
Sodium Chloride Injection USP, 0.9%
0.308 mOsmol/mL
Preservative Free
For use as a sterile diluent
2 mL Single Dose Vial

NDC 0641-0497-25 Rx only
Sodium Chloride Injection USP, 0.9%
0.308 mOsmol/mL
Preservative Free
For use as a sterile diluent
25 x 2 mL Single Dose Vials

PRINCIPAL DISPLAY PANEL

NDC 0641-6144-01
Rx only
Sodium Chloride
Injection USP, 0.9%
0.308 mOsmol/mL
PRESERVATIVE-FREE
For use as a sterile diluent
10 mL Single Dose Vial
Each mL contains sodium
chloride 9 mg in Water for
Injection; pH 4.5-7.0, may
contain hydrochloric acid
and/or sodium hydroxide
for pH adjustment.
Sterile, nonpyrogenic.
Contains no preservative.
Discard unused portion.
For additional information,
see package insert.
Store at 20º-25ºC (68º-77ºF)
[See USP Controlled
Room Temperature].

NDC 0641-6144-25
Rx only
Sodium Chloride
Injection USP, 0.9%
0.308 mOsmol/mL
PRESERVATIVE-FREE
For use as a sterile diluent
25 x 10 mL Single Dose Vials
Each mL contains sodium chloride 9 mg in
Water for Injection; pH 4.5-7.0, may contain
hydrochloric acid and/or sodium hydroxide
for pH adjustment.
Sterile, nonpyrogenic.
Contains no preservative. Discard unused portion.
For additional information, see package insert.
Store at 20º-25ºC (68º-77ºF) [See USP
Controlled Room Temperature].